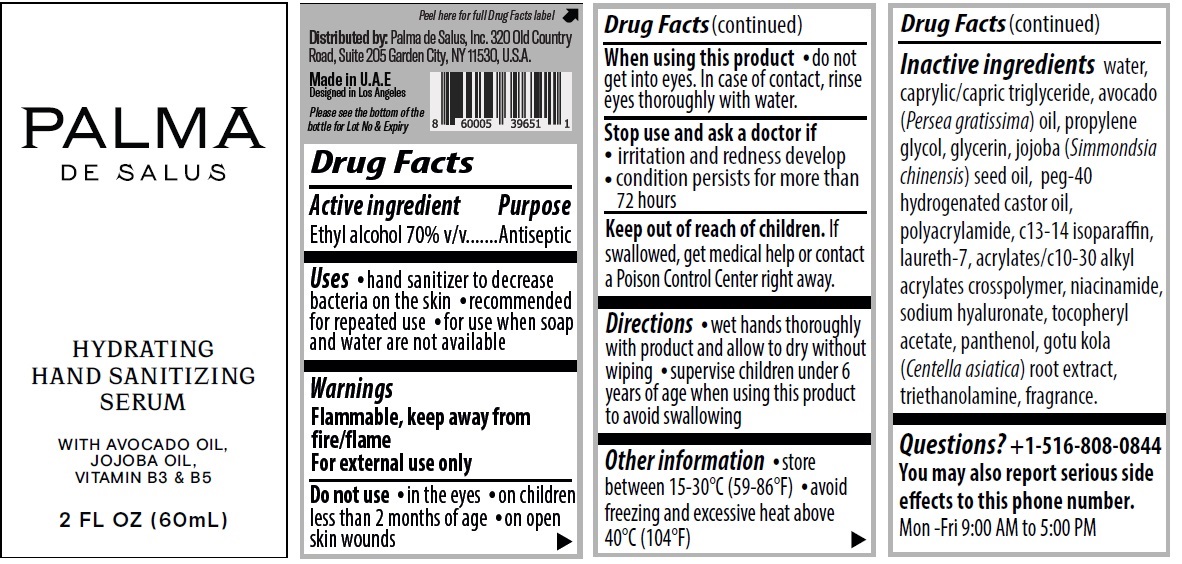 DRUG LABEL: PALMA HYDRATING HAND SANITIZING SERUM
NDC: 81286-102 | Form: LIQUID
Manufacturer: UNITRADE FZE
Category: otc | Type: HUMAN OTC DRUG LABEL
Date: 20241219

ACTIVE INGREDIENTS: ALCOHOL 70 mL/100 mL
INACTIVE INGREDIENTS: WATER; MEDIUM-CHAIN TRIGLYCERIDES; AVOCADO OIL; PROPYLENE GLYCOL; GLYCERIN; JOJOBA OIL; POLYOXYL 40 HYDROGENATED CASTOR OIL; POLYACRYLAMIDE (1500 MW); C13-14 ISOPARAFFIN; LAURETH-7; ACRYLATES/C10-30 ALKYL ACRYLATE CROSSPOLYMER (60000 MPA.S); NIACINAMIDE; HYALURONATE SODIUM; .ALPHA.-TOCOPHEROL ACETATE; PANTHENOL; CENTELLA ASIATICA ROOT; TROLAMINE

PALMA DE SALUS HYDRATING HAND SANITIZING SERUM

Active ingredient

Ethyl alcohol 70% v/v

Purpose

Antiseptic

Uses

• hand sanitizer to decrease bacteria on the skin • recommended for repeated use • for use when soap and water are not available

Warnings

Flammable, keep away from fire/flame
For external use only

Do not use • in the eyes • on children less than 2 months of age • on open skin wounds

When using this product • do not get into eyes. In case of contact, rinse eyes thoroughly with water.

Stop use and ask a doctor if • irritation and redness develop • condition persists for more than 72 hours

Keep out of reach of children. If swallowed, get medical help or contact a Poison Control Center right away.

Directions

• wet hands thoroughly with product and allow to dry without wiping • supervise children under 6 years of age when using this product to avoid swallowing

Other information

• store between 15-30°C (59-86°F) • avoid freezing and excessive heat above 40°C (104°F)

Inactive ingredients

water, caprylic/capric triglyceride, avocado (Persea gratissima) oil, propylene glycol, glycerin, jojoba (Simmondsia chinensis) seed oil, peg-40 hydrogenated castor oil, polyacrylamide, c13-14 isoparaffin, laureth-7, acrylates/c10-30 alkyl acrylates crosspolymer, niacinamide, sodium hyaluronate, tocopheryl acetate, panthenol, gotu kola (Centella asiatica) root extract, triethanolamine, fragrance.

Questions?

+1-516-808-0844
You may also report serious side effects to this phone number.
Mon -Fri 9:00 AM to 5:00 PM

HYDRATING HAND SANITIZING SERUM

WITH AVOCADO OIL, JOJOBA OIL, VITAMIN B3 & B5

Distributed by: Palma de Salus, Inc. 320 Old Country Road, Suite 205 Garden City, NY 11530, U.S.A.

Made in U.A.E
Designed in Los Angeles

Please see the bottom of the bottle for Lot No & Expiry